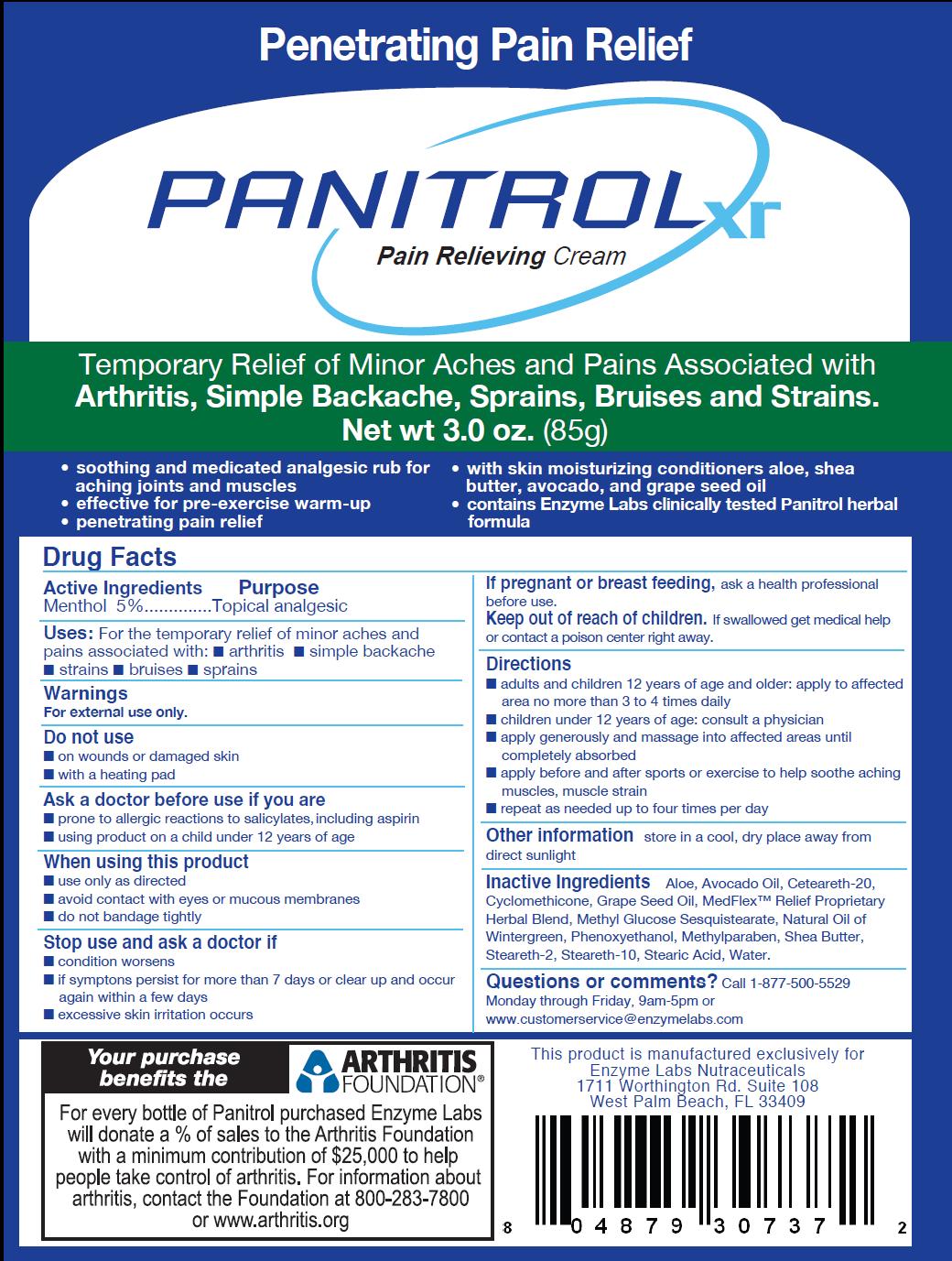 DRUG LABEL: Panitrol
NDC: 59940-001 | Form: CREAM
Manufacturer: Enzyme Labs
Category: otc | Type: HUMAN OTC DRUG LABEL
Date: 20110101

ACTIVE INGREDIENTS: MENTHOL 4.25 g/85 g
INACTIVE INGREDIENTS: ALOE; AVOCADO OIL; CYCLOMETHICONE; GRAPE SEED OIL; METHYL SALICYLATE; PHENOXYETHANOL; METHYLPARABEN; SHEA BUTTER; STEARETH-2; STEARETH-10; STEARIC ACID; WATER

ACTIVE INGREDIENT

Menthol 5%

PURPOSE

Topical analgesic

INDICATIONS AND USAGE

For the temporary relief of minor aches and pains associated with:

- arthritis
- simple backache
- strains
- bruises
- sprains

INACTIVE INGREDIENT

Aloe, Avocado Oil, Ceteareth-20, Cyclomethicone, Grape Seed Oil, MedFlex Relief Proprietary Herbal Blend, Methyl Glucose Sesquistearate, Natural Oil of Wintergreen, Phenoxyethanol, Methylparaben, Shea Butter, Steareth-2, Steareth-10, Stearic Acid, Water

WARNINGS

For external use only.

Do not use

- on wounds or damaged skin
- with a heating pad

Ask a doctor before use if you are

- prone to allergic reactions to salicylates, including aspirin
- using product on a child under 12 years of age

When using this product

- use only as directed
- avoid contact with eyes or mucous membranes
- do not bandage tightly

Stop use and ask a doctor if

- condition worsens
- if symptoms persist for more than 7 days or clear up and occur again within a few days
- excessive skin irritation occurs

PREGNANCY OR BREAST FEEDING

If pregnant or breast feeding, ask a health professional before use.

Keep out of reach of children. If swallowed get medical help or contact a poison center right away.

Directions

- adults and children 12 years of age and older: apply to affected area no more than 3 to 4 times daily
- children under 12 years of age: consult a physician
- apply generously and massage into affected areas until completely absorbed
- apply before and after sports or exercise to help soothe aching muscles, muscle strain
- repeat as needed up to four times per day

STORAGE AND HANDLING

store in a cool, dry place away from direct sunlight

QUESTIONS

Call 1-877-500-5529

Monday through Friday, 9am-5pm or customerservice@enzymelabs.com

PACKAGE LABEL

Penetrating Pain Relief

Temporary Relief of Minor Aches and Pains Associated with Arthritis, Simple Backache, Sprains, Bruises and Strains.

- soothing and medicated analgesic rub for aching joints and muscles
- effective for pre-exercise warm-up
- penetrating pain relief
- with skin moisturizing conditioners aloe, shea butter, avocado, and grape seed oil
- contains Enzyme Labs clinically tested Panitrol herbal formula